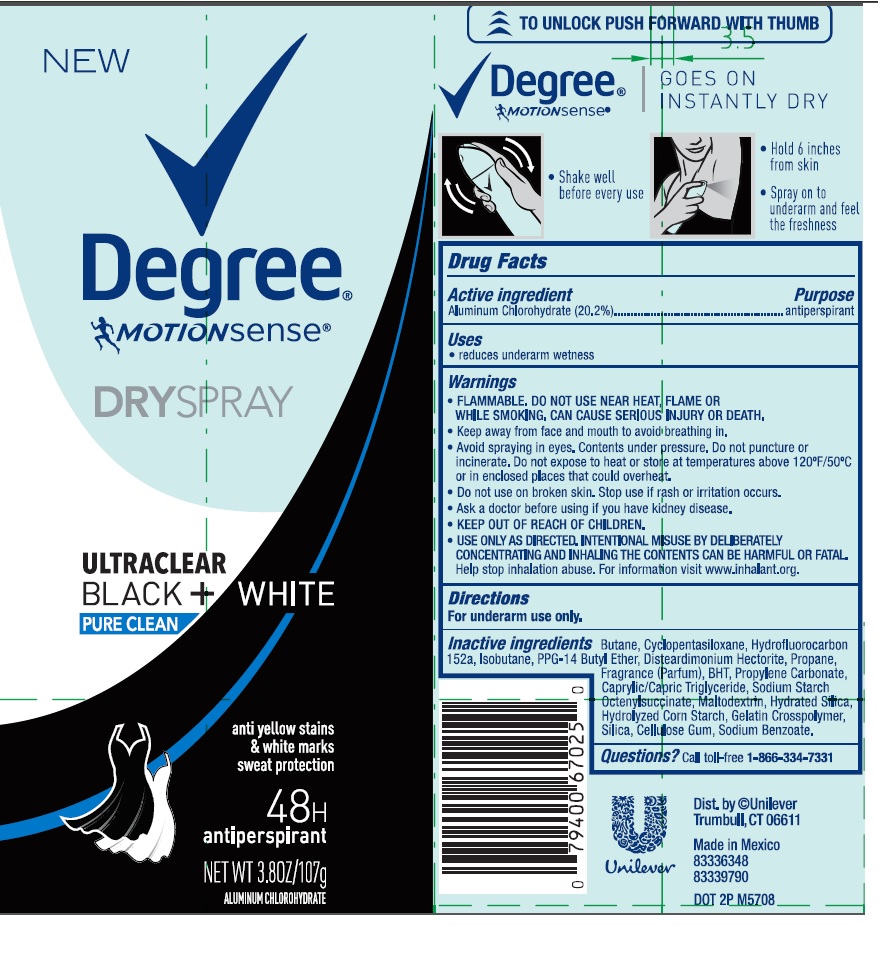 DRUG LABEL: Degree
NDC: 64942-1796 | Form: AEROSOL, SPRAY
Manufacturer: Conopco Inc. d/b/a/ Unilever
Category: otc | Type: HUMAN OTC DRUG LABEL
Date: 20241110

ACTIVE INGREDIENTS: ALUMINUM CHLOROHYDRATE 20.2 g/100 g
INACTIVE INGREDIENTS: BUTANE; CYCLOMETHICONE 5; 1,1-DIFLUOROETHANE; ISOBUTANE; PPG-14 BUTYL ETHER; DISTEARDIMONIUM HECTORITE; PROPANE; BUTYLATED HYDROXYTOLUENE; PROPYLENE CARBONATE; MEDIUM-CHAIN TRIGLYCERIDES; MALTODEXTRIN; HYDRATED SILICA; SILICON DIOXIDE; CARBOXYMETHYLCELLULOSE SODIUM, UNSPECIFIED FORM; SODIUM BENZOATE

Degree-MotionSense Ultraclear Black + White Pure Clean Dry Spray Antiperspirant

Degree MotionSense Ultraclear Black and White Pure Clean Dry Spray Antiperspirant - aluminum chlorohydrate aerosol, spray

Active ingredient

Aluminum Chlorohydrate (20.2%)

Purpose

antiperspirant

Uses

- reduces underarm wetness

Warnings

- FLAMMABLE. DO NOT USE NEAR HEAT, FLAME, OR WHILE SMOKING. CAN CAUSE SERIOUS INJURY OR DEATH
- Keep away from face and mouth to avoid breathing in.
- Avoid spraying in eyes. Contents under pressure. Do not puncture or incinerate. Do not expose to heat or store at temperatures above 120°F/50°C or in enclosed places that could overheat.
- Do not use on broken skin. Stop use if rash or irritation occurs.
- Ask a doctor before using if you have kidney disease.
- USE ONLY AS DIRECTED. INTENTIONAL MISUSE BY DELIBERATELY CONCENTRATING AND INHALING THE CONTENTS CAN BE HARMFUL OR FATAL. Help stop inhalation abuse. For information visit www.inhalant.org

- KEEP OUT OF REACH OF CHILDREN

Directions

For underarm use only

Inactive ingredients

Butane, Cyclopentasiloxane, Hydrofluorocarbon 152a, Isobutane, PPG-14 Butyl Ether, Disteardimonium Hectorite, Propane, Fragrance (Parfum), BHT, Propylene Carbonate, Caprylic/Capric Triglyceride, Sodium Starch Octenylsuccinate, Maltodextrin, Hydrated Silica, Hydrolyzed Corn Starch, Gelatin Crosspolymer, Silica, Cellulose Gum, Sodium Benzoate.

Questions?

Call toll-free 1-866-334-7331